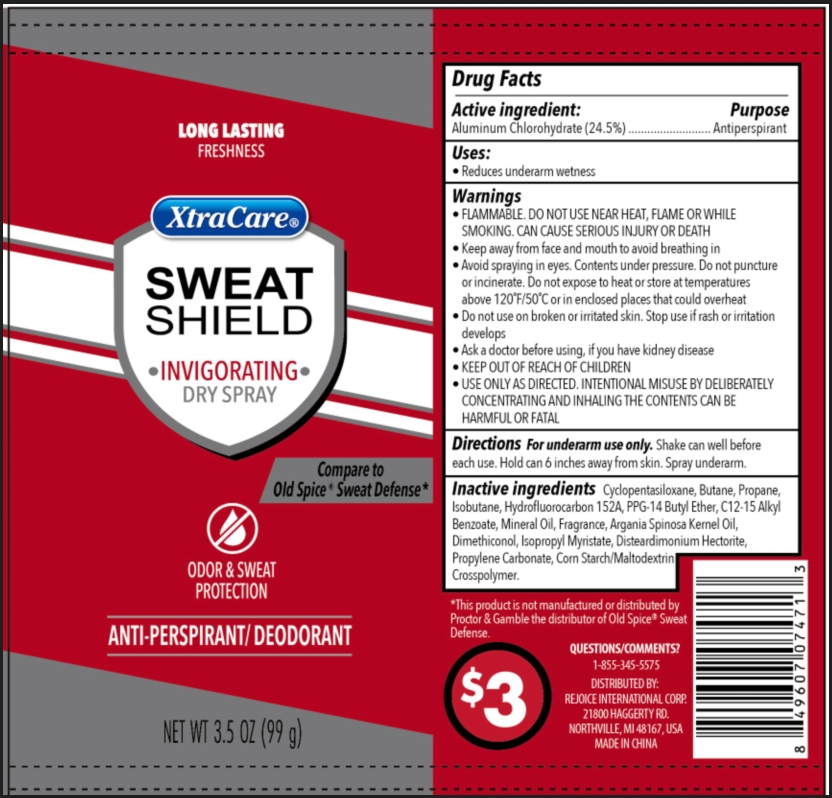 DRUG LABEL: Dry Sweat Shield 3.5oz
NDC: 57337-154 | Form: AEROSOL, SPRAY
Manufacturer: Rejoice International Corp.
Category: otc | Type: HUMAN OTC DRUG LABEL
Date: 20250206

ACTIVE INGREDIENTS: ALUMINUM CHLOROHYDRATE 24.5 g/100 g
INACTIVE INGREDIENTS: PROPANE; ISOBUTANE; 1,1-DIFLUOROETHANE; PPG-14 BUTYL ETHER; CYCLOMETHICONE 5; ISOPROPYL MYRISTATE; STARCH, CORN; PROPYLENE CARBONATE; BUTANE; ALKYL (C12-15) BENZOATE; MINERAL OIL; ARGAN OIL; DIMETHICONE; DISTEARDIMONIUM HECTORITE

Dry Spray Sweat Shield 3.5oz

Active ingredient

Aluminum Chlorohydrate 24.5%

Purpose

Antiperspirant

Uses

Reduces underarm wetness

Warnings

Flammable. Do not use near heat, flame or while smoking. Can cause serious injury or death

When using

- Keep away from face and mouth to avoid breathing in
- Avoid spraying in eyes. Contents under pressure. Do not puncture or incinerate. Do not expose to heat or store at temperatures above 120ºF/50ºC or enclosed places that could overheat.
- USE ONLY AS DIRECTED. INTENTIONAL MISUSE BY DELIBERATELY CONCENTRATING AND INHALING THE CONTENT CAN BE HARMFUL OR FATAL.

Do not use on broken or irritated skin. Stop use if rash or irritation develops.

Keep out of reach of children

Ask a doctor before using, if you have kidney disease.

Directions

For underarm use only. Shake can well before each use. Hold can 6 inches away from skin. Spray underarm.

Inactive ingredients

Cyclopentasiloxane; Butane; Propane;Isobutane; Hydrofluorocarbon 152A; PPG-14 Butyl Ether; C12-15 Alkyl Benzoate; Mineral Oil; Fragrance; Argania Spinosa Kenel Oil; Dimethiconol; Isopropyl Myristate; Disteardimonium Hectorite; Propylene Carbonate; Corn Starch/Maltodextrin Crosspolymer